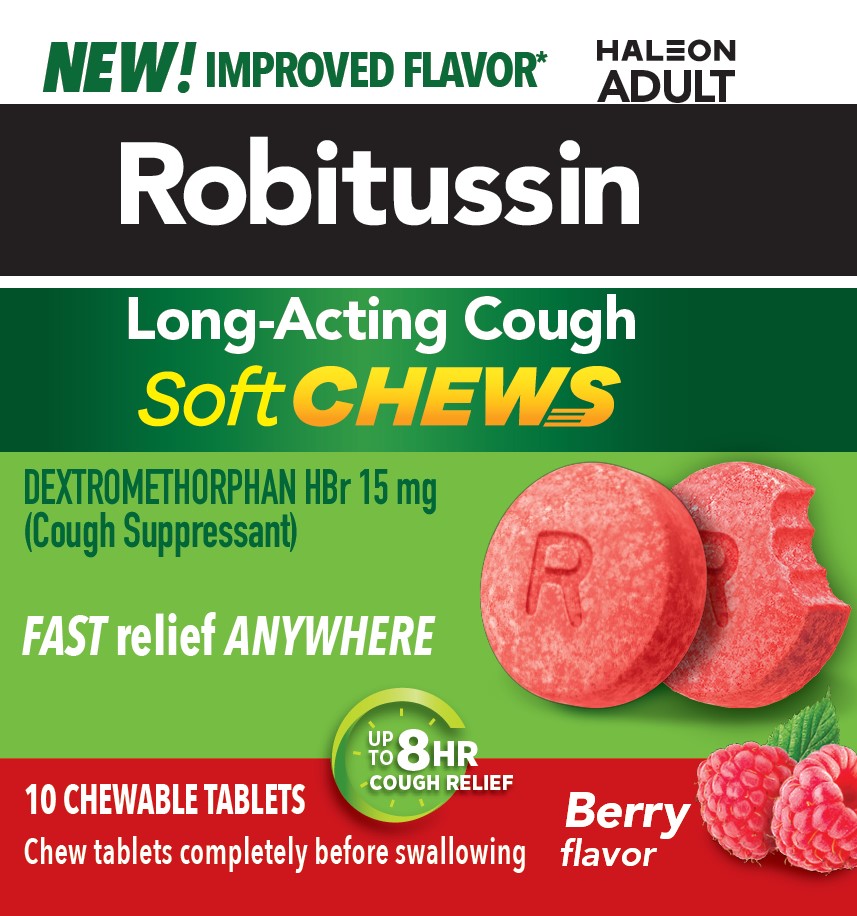 DRUG LABEL: ROBITUSSIN LONG-ACTING COUGH Soft CHEWS
NDC: 0031-9310 | Form: TABLET, CHEWABLE
Manufacturer: Haleon US Holdings LLC
Category: otc | Type: HUMAN OTC DRUG LABEL
Date: 20251125

ACTIVE INGREDIENTS: DEXTROMETHORPHAN HYDROBROMIDE 15 mg/1 1
INACTIVE INGREDIENTS: CALCIUM GLUCONATE MONOHYDRATE; CARBOXYMETHYLCELLULOSE CALCIUM; CARNAUBA WAX; CORN SYRUP; CROSPOVIDONE, UNSPECIFIED; FD&C RED NO. 40; GLYCERIN; MANNITOL; STARCH, CORN; DIMETHICONE, UNSPECIFIED; SODIUM GLUCONATE; SORBITOL; SORBITOL SOLUTION; SUCRALOSE; SUCROSE; COW MILK

Drug Facts

Active ingredient (in each chewable tablet)

Dextromethorphan equivalent to 15 mg dextromethorphan HBr

Purpose

Cough suppressant

Use

- temporarily relieves cough due to minor throat and bronchial irritation as may occur with a cold

Warnings

DO NOT USE

Do not useif you are now taking a prescription monoamine oxidase inhibitor (MAOI) (certain drugs for depression, psychiatric, or emotional conditions, or Parkinson's disease), or for 2 weeks after stopping the MAOI drug. If you do not know if your prescription drug contains an MAOI, ask a doctor or pharmacist before taking this product.

Ask a doctor before use if you have

- cough that occurs with too much phlegm (mucus)
- cough that lasts or is chronic such as occurs with smoking, asthma, or emphysema

Stop use and ask a doctor ifcough lasts more than 7 days, comes back, or is accompanied by fever, rash, or persistent headache. These could be signs of a serious condition.

PREGNANCY OR BREAST FEEDING

If pregnant or breast-feeding,ask a health professional before use.

Keep out of reach of children.In case of overdose, get medical help or contact a Poison Control Center right away.

Directions

- do not take more than 4 doses (8 chewable tablets) in 24-hours, unless directed by a doctor
- chew tablets completely before swalloing
- this adult product is not intended for use in children under 12 years of age

age |  | dose
adults and children; 12 years and over |  | take 2 chewable tablets every 6 to 8 hours, as needed
children under 12 years |  | do not use

Other information

- each chewable tablet contains:calcium 10 mg, potassium 10 mg, sodium 6 mg
- store at a controlled room temperature 20-25°C (68-77°F)

Inactive ingredients

calcium gluconate monohydrate, carboxymethylcellulose calcium, carnauba wax, corn syrup solids, crospovidone, FD&C red no. 40, glycerin, mannitol, natural and artificial flavors, pregelatinized starch, simethicone, sodium gluconate, sorbitol, sorbitol solution, sucralose, sucrose, whole dry milk

Questions or comments?

call weekdays from 8 AM to 6 PM EST at 1-855-297-3031

Additional Information

Do Not Use if seal under bottle cap imprinted with “SEALED for YOUR PROTECTION” is broken or missing.

*Among those with a preference vs. original formulation.

PARENTS:

Learn about teen medicine abuse

www.StopMedicineabuse.org

PRINCIPAL DISPLAY PANEL

NEW!IMPROVED FLAVOR*

Robitussin

Long-Acting Cough

Soft CHEWS

DEXTROMETHORPHAN HBr 15 mg
(Cough Suppressant)

FASTrelief ANYWHERE

UP TO 8HRCOUGH RELIEF

10 CHEWABLE TABLETS

Chew tablets completely before swallowing

Berry flavor